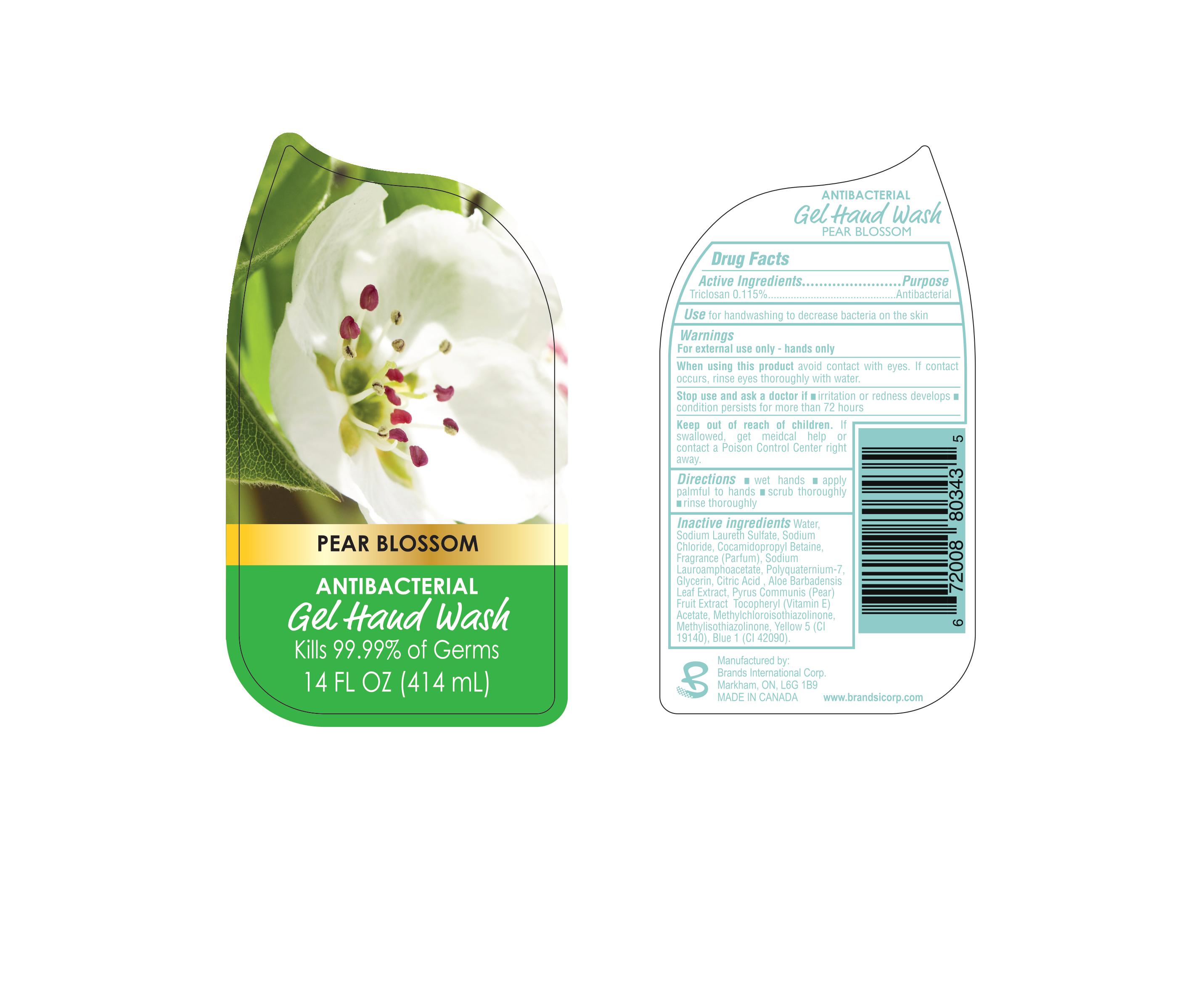 DRUG LABEL: Pear Blossom Antibacterial Gel Hand Wash
NDC: 50157-118 | Form: LIQUID
Manufacturer: Brands International
Category: otc | Type: HUMAN OTC DRUG LABEL
Date: 20160203

ACTIVE INGREDIENTS: TRICLOSAN 1.15 mg/1 mL
INACTIVE INGREDIENTS: METHYLCHLOROISOTHIAZOLINONE; METHYLISOTHIAZOLINONE; FD&C YELLOW NO. 5; .ALPHA.-TOCOPHEROL ACETATE; WATER; FD&C BLUE NO. 1; COCAMIDOPROPYL BETAINE; SODIUM LAUROAMPHOACETATE; POLYQUATERNIUM-7 (70/30 ACRYLAMIDE/DADMAC; 2600000 MW); GLYCERIN; ALOE VERA LEAF; PEAR; SODIUM LAURETH SULFATE; SODIUM CHLORIDE; ANHYDROUS CITRIC ACID

Pear Blossom Antibacterial Gel Hand Wash

Drug Facts

Active Ingredient

Triclosan 0.115%

Purpose

Antibacterial

WARNINGS

For external use only - hands only

When using this product avoid contact with eyes. If contact occurs, rinse eyes thoroughly with water

Stop use and ask a doctor if

- Irritation or redness develops
- condition persists for more than 72 hours

KEEP OUT OF REACH OF CHILDREN

If swallowed, get medical help or contact a Poison Control Center right away

Directions

- wet hands
- apply palmful to hands
- scrub throughly
- rinse throughly

Inactive Ingredients

Water, Sodium Laureth Sulfate, Sodium Chloride, Cocamidopropyl Betaine, Fragrance (Parfum), Sodium Lauroamphoacetate, Polyquaternium 7, Glycerin, Citric Acid, Aloe Barbadensis Leaf Extract, Pyrus Communis (Pear) Fruit Extract, Tocopheryl (Vitamin E) Acetate, Methylchloroisothiazolinone, Methylisothiazolinone, Yellow 5 (Cl 19140), Blue 1 (Cl 42090)

Uses

for handwashing or decrease bacteria to the skin

PACKAGE LABEL

PEAR BLOSSOM

ANTIBACTERIAL

Gel Hand Wash

Kills 99.99% of Germs

14 FL OZ (414 mL)